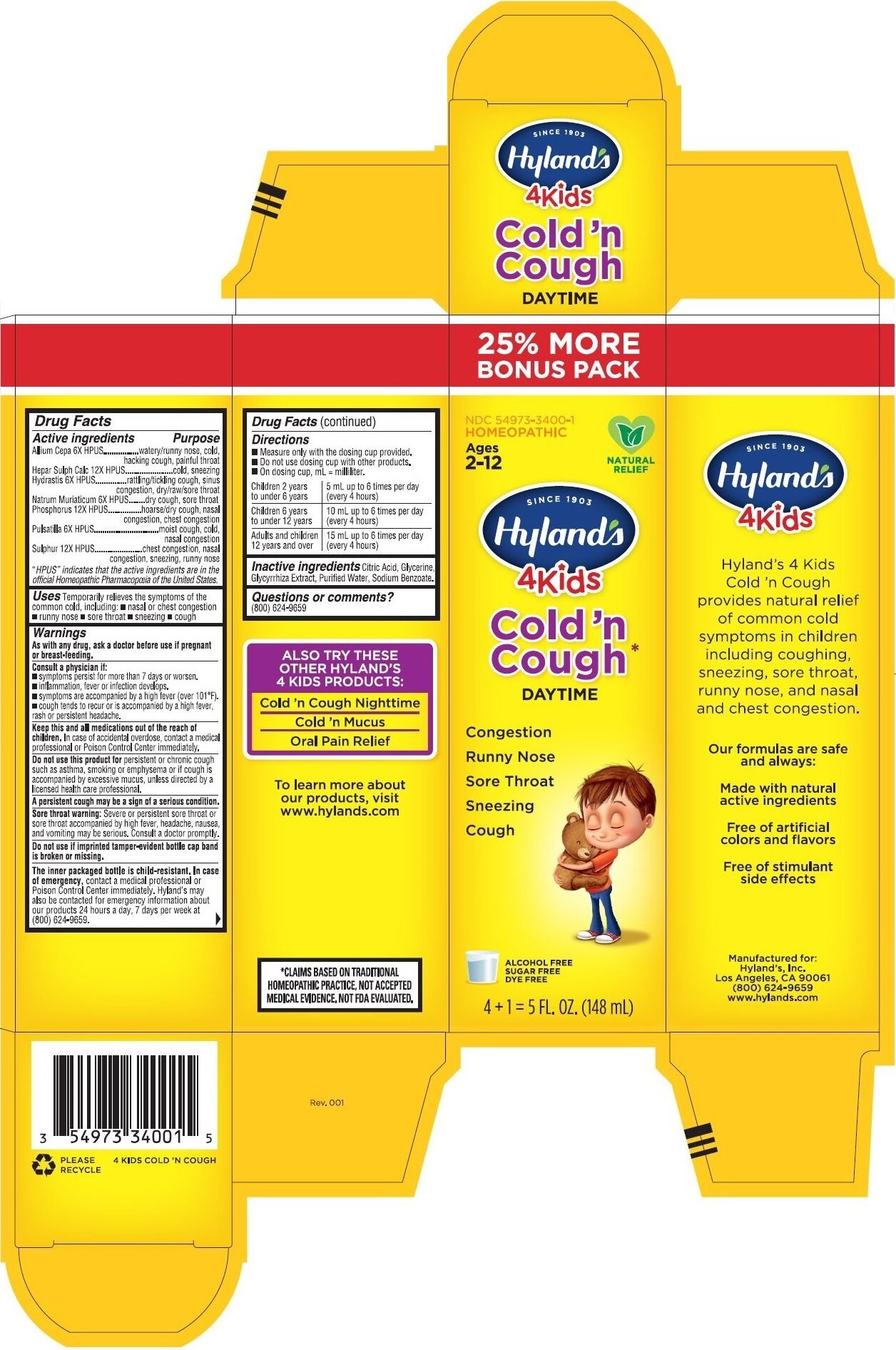 DRUG LABEL: 4 Kids Cold and Cough Daytime
NDC: 54973-3400 | Form: LIQUID
Manufacturer: Hyland's Inc.
Category: homeopathic | Type: HUMAN OTC DRUG LABEL
Date: 20251219

ACTIVE INGREDIENTS: CALCIUM SULFIDE 12 [hp_X]/1 mL; SODIUM CHLORIDE 6 [hp_X]/1 mL; SULFUR 12 [hp_X]/1 mL; PHOSPHORUS 12 [hp_X]/1 mL; ANEMONE PULSATILLA 6 [hp_X]/1 mL; GOLDENSEAL 6 [hp_X]/1 mL; ONION 6 [hp_X]/1 mL
INACTIVE INGREDIENTS: WATER; CITRIC ACID MONOHYDRATE; GLYCYRRHIZA GLABRA; SODIUM BENZOATE; GLYCERIN

4 Kids Cold 'n Cough Daytime

Drugs Facts

Active ingredients

Allium Cepa 6X HPUS

Hepar Sulph Calc 12X HPUS

Hydrastis 6X HPUS

Natrum Muriaticum 6X HPUS

Phosphorus 12X HPUS

Pulsatilla 6X HPUS

Sulphur 12X HPUS

"HPUS" indicates that the active ingredients are in the official Homeopathic Pharmacopœia of the United States.

Purpose

Allium Cepa 6X HPUS..........................watery/runny nose, cold, hacking cough, painful throat

Hepar Sulph Calc 12X HPUS................cold, sneezing

Hydrastis 6X HPUS................................rattling/tickling cough, sinus congestion, dry/raw/sore throat

Natrum Muriaticum 6X HPUS................dry cough, sore throat

Phosphorus 12X HPUS.........................hoarse/dry cough, nasal congestion, chest congestion

Pulsatilla 6X HPUS................................moist cough, cold, nasal congestion

Sulphur 12X HPUS................................chest congestion, nasal congestion, sneezing, runny nose

Uses

Temporarily relieves the symptoms of the common cold including: nasal or chest congestion, runny nose, sore throat, sneezing, cough.

Warnings

PREGNANCY OR BREAST FEEDING

As with any drug, ask a doctor before use if pregnant or breast-feeding.

Consult a physician if

- Symptoms persist for more than 7 days or worsen
- Inflammation, fever or infection develops
- Symptoms are accompanied by high fever (101°F).
- Cough tends to recur or is accompanied by high fever, rash or persistent headache

Keep this and all medications out of the reach of children

In case of accidental overdose, contact a medical professional or Poison Control Center immediately.

Do not use this product

For persistent or chronic cough such as asthma, smoking or emphysema or if cough is accompanied by excessive mucus, unless directed by a licensed medical professional.

Sore throat warning

Severe or persistent sore throat or sore throat accompanied by high fever, headache, nausea and vomiting may be serious. Consult a doctor promptly.

The inner packaged bottle is child-resistant

In case of emergency

contact a medical professional or Poison Control Center immediately. Hyland's may also be contacted for emergency information about our products 24 hours a day, 7 days per week at (800) 624-9659.

Drug Facts(continued)

Directions

- Measure only with the dosing cup provided
- Do not use dosing cup with other products
- On dosing cup, mL = milliliter, tsp = teaspoon

Children 2 years to; under 6 years | 5 mL or 1 teaspoon up to 6; times per day (every 4 hours)
Children 6 years to; under 12 years | 10 mL or 2 teaspoons up to 6; times per day (every 4 hours)
Adults and children; 12 years and over | 15 mL or 3 teaspoons up to 6; times per day (every 4 hours)

Inactive ingredients

Citric Acid, Glycerine, Glycyrrhiza Extract, Purified Water, Sodium Benzoate.

Questions or comments?

(800) 624-9659

Principal Display Panel - 148 mL Bottle Carton

25% MORE

BONUS PACK

NDC 54973-3400-1

HOMEOPATHIC

Ages

2-12

NATURAL

RELIEF

SINCE 1903

Hyland's

4Kiids

Cold 'n

Cough*

DAYTIME

Congestion

Runny Nose

Sore Throat

Sneezing

Cough

ALCOHOL FREE

SUGAR FREE

DYE FREE

4 + 1 = 5 S FL. OZ. (148 mL)